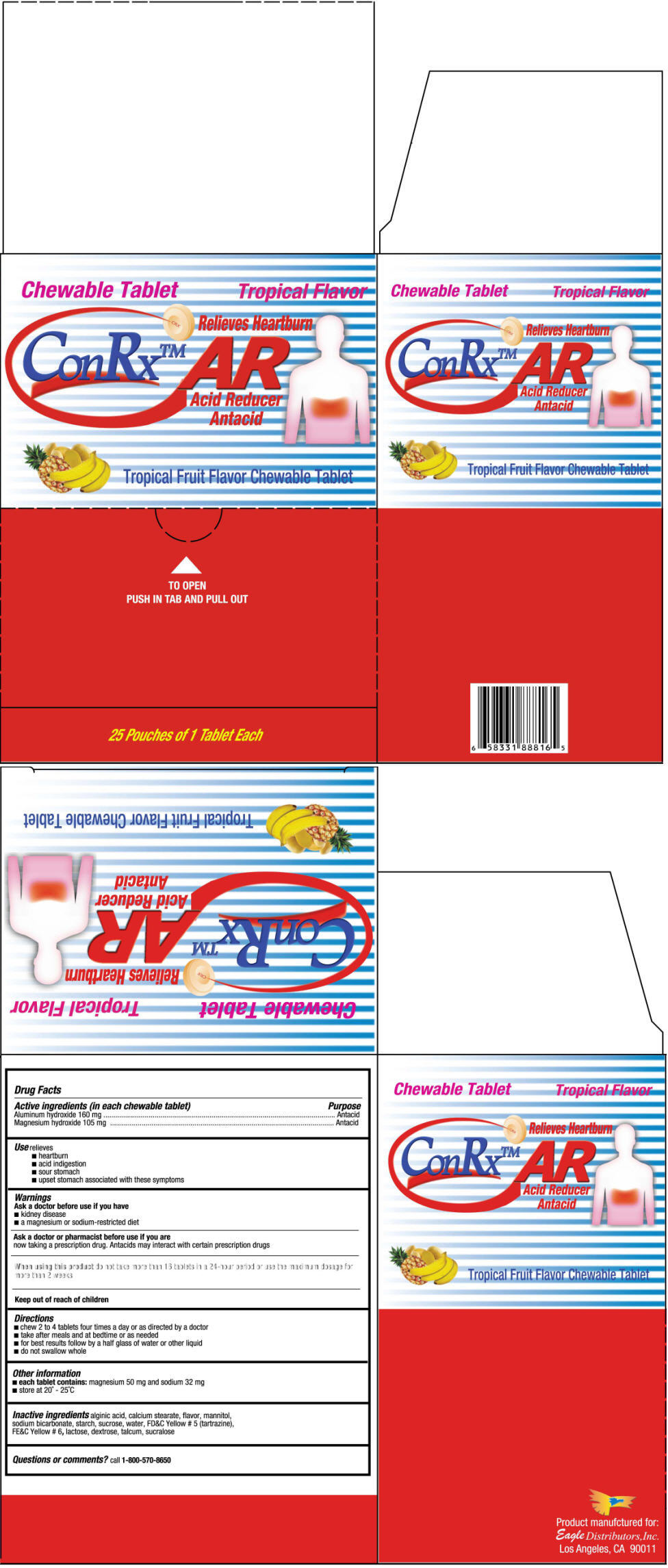 DRUG LABEL: ConRx AR
NDC: 68737-237 | Form: TABLET, CHEWABLE
Manufacturer: Eagle Distributors,Inc.
Category: otc | Type: HUMAN OTC DRUG LABEL
Date: 20130314

ACTIVE INGREDIENTS: ALUMINUM HYDROXIDE 160 mg/1 1; MAGNESIUM HYDROXIDE 105 mg/1 1
INACTIVE INGREDIENTS: ALGINIC ACID; CALCIUM STEARATE; MANNITOL; SODIUM BICARBONATE; STARCH, CORN; WATER; SUCROSE; FD&C YELLOW NO. 5; FD&C YELLOW NO. 6; LACTOSE; DEXTROSE; TALC; SUCRALOSE

ConRx™ AR

Drug Facts

ACTIVE INGREDIENT

Active ingredients (in each chewable tablet) | Purpose
Aluminum hydroxide 160 mg | Antacid
Magnesium hydroxide 105 mg | Antacid

Use

- heartburn
- acid indiestion
- sour stomach
- upset stomch associated with these symptoms

Warnings

Ask a doctor before use if you have

- kidney disease
- a magnesium or sodium-restricted diet

Ask a doctor or pharmacist before use if you are

now taking a prescription durg. Antacids may interact with certain prescription drugs

When using this product do not take more than 16 tablets in a 24-hour period or use the Maximum dosage for more than 2 wekks

Keep out of reach of children.

Directions

- chew 2 to 4 tablets four times a day or as directed by a doctor
- take after meals and at bedtime or as needed
- for best results follow by a half glass of water or other liquid
- do not swallow whole

Other information

- each tablet contains: magnesium 50 mg and sodium 32 mg
- store at 20°-25°C

Inactive ingredients

alginic acid, calcium stearate, flavor, mannitol, sodium bicarbonate, starch, sucrose, water, FD&C Yellow # 5 (tartrazine), FE&C Yellow # 6, lactose, dextrose, talcum, sucralose

Questions or comments?

1-800-570-8650

PRINCIPAL DISPLAY PANEL - 50 Pouch Box

Chewable Tablet
Tropical Flavor

Relieves Heartburn

ConRx™ AR

Acid Reducer
Antacid

Tropical Fruit Flavor Chewable Tablet

TO OPEN
PUSH IN TAB AND PULL OUT

25 Pouches of 1 Tablet Each